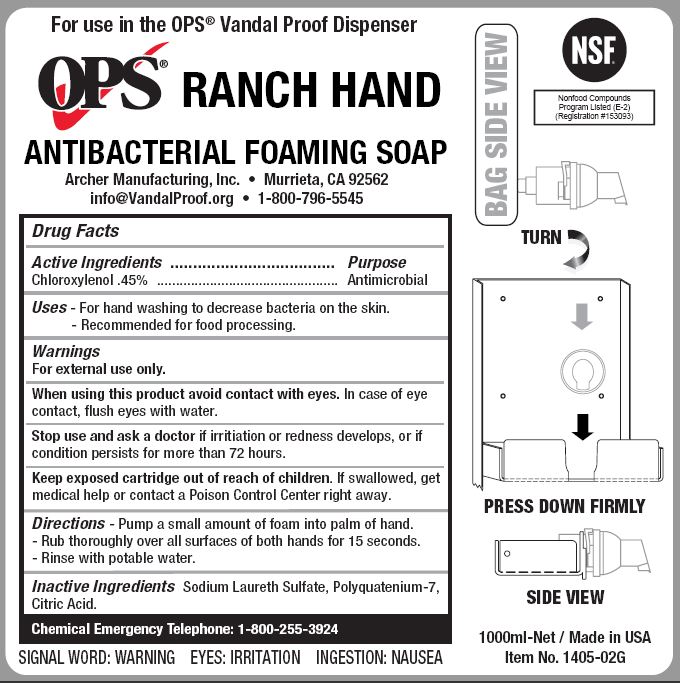 DRUG LABEL: OPS RANCH HAND ANTIBACTERIAL FOAMING
NDC: 79016-141 | Form: SOAP
Manufacturer: Archer Manufacturing, Inc.
Category: otc | Type: HUMAN OTC DRUG LABEL
Date: 20241205

ACTIVE INGREDIENTS: CHLOROXYLENOL 0.45 g/100 mL
INACTIVE INGREDIENTS: ANHYDROUS CITRIC ACID; SODIUM LAURETH SULFATE; POLYQUATERNIUM-7 (70/30 ACRYLAMIDE/DADMAC; 1600 KD)

ARCHER - OPS RANCH HAND ANTIBACTERIAL FOAMING SOAP (79016-141)

ACTIVE INGREDIENT

CHLOROXYLENOL 0.45%

PURPOSE

Antimicrobial

USES

- For hand washing to decrease bacteria on skin.
- Recommended for repeated use.

WARNINGS

For external use only.

When using this product avoid contact with eyes. In case of eye contact, flush eyes with water.

Stop use and ask a doctor if irritation or redness develops, or if condition persists for more than 72 hours.

KEEP OUT OF REACH OF CHILDREN

Keep exposed cartridge out of reach of children. If swallowed, get medical help or contact a Poison Control Center right away.

DIRECTIONS

- Pump a small amount of foam into palm of hand.
- Rub thoroughly over all surfaces of both hands for 15 seconds.
- Rinse with potable water.

INACTIVE INGREDIENTS

Sodium Laureth Sulfate, Polyquatenium-7, Citric Acid.